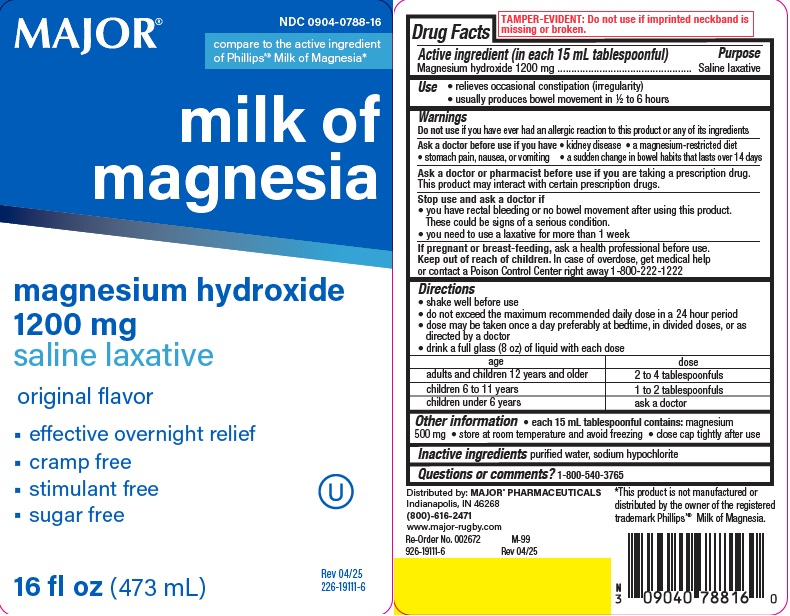 DRUG LABEL: MILK OF MAGNESIA ORIGINAL
NDC: 0904-0788 | Form: LIQUID
Manufacturer: MAJOR Pharmaceuticals Inc.
Category: otc | Type: HUMAN OTC DRUG LABEL
Date: 20251211

ACTIVE INGREDIENTS: MAGNESIUM HYDROXIDE 1200 mg/15 mL
INACTIVE INGREDIENTS: WATER; SODIUM HYPOCHLORITE

major mom

Active ingredient (in each 15 mL tablespoonful)

Magnesium hydroxide 1200 mg

Purpose

Saline laxative

Use

- relieves occasional constipation (irregularity)
- usually produces bowel movement in 1/2 to 6 hours

Warnings

Do not use if you have ever had an allergic reaction to this product or any of its ingredients

Ask a doctor before use if you have

- kidney disease
- a magnesium-restricted diet
- stomach pain, nausea, or vomiting
- a sudden change in bowel habits that lasts over 14 days

Ask a doctor or pharmacist before use if you are taking a prescription drug.

This product may interact with certain prescription drugs.

Stop use and ask a doctor if

- you have rectal bleeding or no bowel movement after using this product. These could be signs of a serious condition.
- you need to use a laxative for more than 1 week

If pregnant or breast-feeding, ask a health professional before use.

Keep out of reach of children. In case of overdose, get medical help or contact a
Poison Control Center right away 1-800-222-1222.

Directions

- shake well before use
- do not exceed the maximum recommended daily dose in a 24 hour period
- dose may be taken once a day preferably at bedtime, in divided doses, or as directed by a doctor
- drink a full glass (8 oz) of liquid with each dose

age | dose
adults and children 12 years and older | 2 to 4 tablespoonfuls
children 6 to 11 years | 1 to 2 tablespoonfuls
children under 6 years | ask a doctor

Other information

- each 15 mL contains: magnesium 500 mg
- store at room temperature and avoid freezing
- close cap tightly after use

Inactive ingredients

purified water, sodium hypochlorite

Questions or comments?

1-800-540-3765